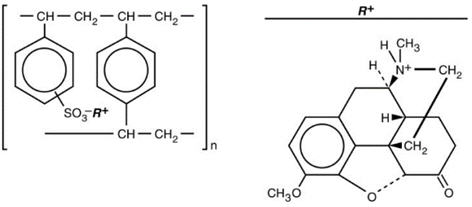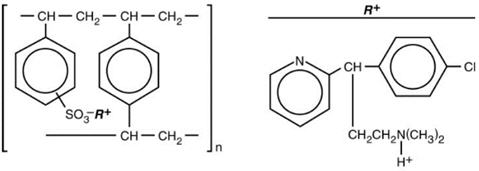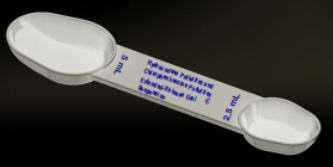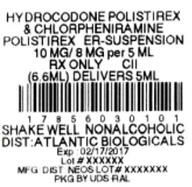 DRUG LABEL: Hydrocodone Polistirex and Chlorpheniramine Polistirex
NDC: 17856-0301 | Form: SUSPENSION, EXTENDED RELEASE
Manufacturer: Atlantic Biologicals Corps
Category: prescription | Type: HUMAN PRESCRIPTION DRUG LABEL
Date: 20170616
DEA Schedule: CII

ACTIVE INGREDIENTS: HYDROCODONE 10 mg/5 mL; CHLORPHENIRAMINE 8 mg/5 mL
INACTIVE INGREDIENTS: Water; High Fructose Corn Syrup; Sucrose; Propylene Glycol; Xanthan Gum; Corn Oil; Methylparaben; Polysorbate 80; Ascorbic Acid; Propylparaben; ETHYLCELLULOSE, UNSPECIFIED; Sorbitol; Dibutyl Sebacate; D&C Yellow No. 10; FD&C Yellow No. 6; Sodium Benzoate; Phosphoric Acid

Hydrocodone Polistirex and Chlorpheniramine Polistirex
Extended-Release Oral Suspension
CII

Rx Only

DESCRIPTION

Each 5 mL of Hydrocodone Polistirex and Chlorpheniramine Polistirex Extended-Release Oral Suspension contains hydrocodone polistirex equivalent to 10 mg of hydrocodone bitartrate and chlorpheniramine polistirex equivalent to 8 mg of chlorpheniramine maleate. Hydrocodone is a centrally-acting narcotic antitussive. Chlorpheniramine is an antihistamine. Hydrocodone Polistirex and Chlorpheniramine Polistirex Extended-Release Oral Suspension is for oral use only.

Hydrocodone Polistirex: Sulfonated styrene-divinylbenzene copolymer complex with 4,5 α-epoxy-3-methoxy-17-methylmorphinan-6-one.

Chlorpheniramine Polistirex: Sulfonated styrene-divinylbenzene copolymer complex with 2-[p-chloro-α-[2-(dimethylamino)ethyl]-benzyl]pyridine.

Inactive Ingredients: Purified Water, High Fructose Corn Syrup, Sucrose, Propylene Glycol, Xanthan Gum, Vegetable (Corn) Oil, Methylparaben, Polysorbate 80, Ascorbic Acid, Propylparaben, Ethylcellulose, Sorbitol, Dibutyl Sebacate, Natural Mango Flavor, D&C Yellow No. 10, FD&C Yellow No. 6, Sodium Benzoate, and Phosphoric Acid.

CLINICAL PHARMACOLOGY

Hydrocodone is a semisynthetic narcotic antitussive and analgesic with multiple actions qualitatively similar to those of codeine. The precise mechanism of action of hydrocodone and other opiates is not known; however, hydrocodone is believed to act directly on the cough center. In excessive doses, hydrocodone, like other opium derivatives, will depress respiration. The effects of hydrocodone in therapeutic doses on the cardiovascular system are insignificant. Hydrocodone can produce miosis, euphoria, and physical and psychological dependence.

Chlorpheniramine is an antihistamine drug (H1 receptor antagonist) that also possesses anticholinergic and sedative activity. It prevents released histamine from dilating capillaries and causing edema of the respiratory mucosa.

Hydrocodone release from Hydrocodone Polistirex and Chlorpheniramine Polistirex Extended-Release Oral Suspension is controlled by an extended-release drug delivery system, which combines an ion-exchange polymer matrix with a diffusion rate-limiting permeable coating. Chlorpheniramine release is prolonged by use of an ion-exchange polymer system.

Following multiple dosing with Hydrocodone Polistirex and Chlorpheniramine Polistirex Extended-Release Oral Suspension products, hydrocodone mean (S.D.) peak plasma concentrations of 22.8 (5.9) ng/mL occurred at 3.4 hours. Chlorpheniramine mean (S.D.) peak plasma concentrations of 58.4 (14.7) ng/mL occurred at 6.3 hours following multiple dosing. Peak plasma levels obtained with an immediate-release syrup occurred at approximately 1.5 hours for hydrocodone and 2.8 hours for chlorpheniramine. The plasma half-lives of hydrocodone and chlorpheniramine have been reported to be approximately 4 and 16 hours, respectively.

INDICATIONS AND USAGE

Hydrocodone Polistirex and Chlorpheniramine Polistirex Extended-Release Oral Suspension is indicated for relief of cough and upper respiratory symptoms associated with allergy or a cold in adults and children 6 years of age and older.

CONTRAINDICATIONS

Hydrocodone Polistirex and Chlorpheniramine Polistirex Extended-Release Oral Suspension is contraindicated in patients with a known allergy or sensitivity to hydrocodone or chlorpheniramine.

The use of Hydrocodone Polistirex and Chlorpheniramine Polistirex Extended-Release Oral Suspension is contraindicated in children less than 6 years of age due to the risk of fatal respiratory depression.

WARNINGS

Respiratory Depression

As with all narcotics, Hydrocodone Polistirex and Chlorpheniramine Polistirex Extended-Release Oral Suspension produces dose-related respiratory depression by directly acting on brain stem respiratory centers. Hydrocodone affects the center that controls respiratory rhythm and may produce irregular and periodic breathing. Caution should be exercised when Hydrocodone Polistirex and Chlorpheniramine Polistirex Extended-Release Oral Suspension is used postoperatively and in patients with pulmonary disease, or whenever ventilatory function is depressed. If respiratory depression occurs, it may be antagonized by the use of naloxone hydrochloride and other supportive measures when indicated (see OVERDOSAGE).

Head Injury and Increased Intracranial Pressure

The respiratory depressant effects of narcotics and their capacity to elevate cerebrospinal fluid pressure may be markedly exaggerated in the presence of head injury, other intracranial lesions, or a pre-existing increase in intracranial pressure. Furthermore, narcotics produce adverse reactions, which may obscure the clinical course of patients with head injuries.

Acute Abdominal Conditions

The administration of narcotics may obscure the diagnosis or clinical course of patients with acute abdominal conditions.

Obstructive Bowel Disease

Chronic use of narcotics may result in obstructive bowel disease especially in patients with underlying intestinal motility disorder.

Pediatric Use

The use of Hydrocodone Polistirex and Chlorpheniramine Polistirex Extended-Release Oral Suspension is contraindicated in children less than 6 years of age (see CONTRAINDICATIONS).

In pediatric patients, as well as adults, the respiratory center is sensitive to the depressant action of narcotic cough suppressants in a dose-dependent manner. Caution should be exercised when administering Hydrocodone Polistirex and Chlorpheniramine Polistirex Extended-Release Oral Suspension to pediatric patients 6 years of age and older. Overdose or concomitant administration of Hydrocodone Polistirex and Chlorpheniramine Polistirex Extended-Release Oral Suspension with other respiratory depressants may increase the risk of respiratory depression in pediatric patients. Benefit to risk ratio should be carefully considered, especially in pediatric patients with respiratory embarrassment (e.g., croup) (see PRECAUTIONS).

PRECAUTIONS

General

Caution is advised when prescribing this drug to patients with narrow-angle glaucoma, asthma, or prostatic hypertrophy.

Special Risk Patients

As with any narcotic agent, Hydrocodone Polistirex and Chlorpheniramine Polistirex Extended-Release Oral Suspension should be used with caution in elderly or debilitated patients and those with severe impairment of hepatic or renal function, hypothyroidism, Addison's disease, prostatic hypertrophy, or urethral stricture. The usual precautions should be observed and the possibility of respiratory depression should be kept in mind.

Information for Patients

Patients should be advised that Hydrocodone Polistirex and Chlorpheniramine Polistirex Extended-Release Oral Suspension may produce marked drowsiness and impair the mental and/or physical abilities required for the performance of potentially hazardous tasks such as driving a car or operating machinery.

Hydrocodone Polistirex and Chlorpheniramine Polistirex Extended-Release Oral Suspension must not be diluted with fluids or mixed with other drugs as this may alter the resin-binding and change the absorption rate, possibly increasing the toxicity.

Patients should be advised to measure Hydrocodone Polistirex and Chlorpheniramine Polistirex Extended-Release Oral Suspension with an accurate measuring device. A household teaspoon is not an accurate measuring device and could lead to overdosage. A pharmacist can recommend an appropriate measuring device and can provide instructions for measuring the correct dose.

A dosing spoon is provided with the 4 oz (118 mL) packaged product. One side of the spoon is for a 2.5 mL dose. The other side of the spoon is for a 5 mL dose. Instruct the patient to fill to level the side of the spoon for the dose that has been prescribed. The spoon should not be overfilled. Rinse the measuring device or dosing spoon after each use.

Shake well before using.

Keep out of the reach of children.

Cough Reflex

Hydrocodone suppresses the cough reflex; as with all narcotics, caution should be exercised when Hydrocodone Polistirex and Chlorpheniramine Polistirex Extended-Release Oral Suspension is used postoperatively, and in patients with pulmonary disease.

Drug Interactions

Patients receiving narcotics, antihistaminics, antipsychotics, antianxiety agents, or other CNS depressants (including alcohol) concomitantly with Hydrocodone Polistirex and Chlorpheniramine Polistirex Extended-Release Oral Suspension may exhibit an additive CNS depression. When combined therapy is contemplated, the dose of one or both agents should be reduced.

The use of MAO inhibitors or tricyclic antidepressants with hydrocodone preparations may increase the effect of either the antidepressant or hydrocodone.

The concurrent use of other anticholinergics with hydrocodone may produce paralytic ileus.

Carcinogenesis, Mutagenesis, Impairment of Fertility

Carcinogenicity, mutagenicity, and reproductive studies have not been conducted with Hydrocodone Polistirex and Chlorpheniramine Polistirex Extended-Release Oral Suspension.

Pregnancy

Teratogenic Effects

Pregnancy Category C

Hydrocodone has been shown to be teratogenic in hamsters when given in doses 700 times the human dose. There are no adequate and well-controlled studies in pregnant women. Hydrocodone Polistirex and Chlorpheniramine Polistirex Extended-Release Oral Suspension should be used during pregnancy only if the potential benefit justifies the potential risk to the fetus.

Nonteratogenic Effects

Babies born to mothers who have been taking opioids regularly prior to delivery will be physically dependent. The withdrawal signs include irritability and excessive crying, tremors, hyperactive reflexes, increased respiratory rate, increased stools, sneezing, yawning, vomiting, and fever. The intensity of the syndrome does not always correlate with the duration of maternal opioid use or dose.

Labor and Delivery

As with all narcotics, administration of Hydrocodone Polistirex and Chlorpheniramine Polistirex Extended-Release Oral Suspension to the mother shortly before delivery may result in some degree of respiratory depression in the newborn, especially if higher doses are used.

Nursing Mothers

It is not known whether this drug is excreted in human milk. Because many drugs are excreted in human milk and because of the potential for serious adverse reactions in nursing infants from Hydrocodone Polistirex and Chlorpheniramine Polistirex Extended-Release Oral Suspension, a decision should be made whether to discontinue nursing or to discontinue the drug, taking into account the importance of the drug to the mother.

Pediatric Use

The use of Hydrocodone Polistirex and Chlorpheniramine Polistirex Extended-Release Oral Suspension is contraindicated in children less than 6 years of age (see CONTRAINDICATIONS and ADVERSE REACTIONS, Respiratory, Thoracic and Mediastinal Disorders).

Hydrocodone Polistirex and Chlorpheniramine Polistirex Extended-Release Oral Suspension should be used with caution in pediatric patients 6 years of age and older (see WARNINGS, Pediatric Use).

Geriatric Use

Clinical studies of Hydrocodone Polistirex and Chlorpheniramine Polistirex Extended-Release Oral Suspension did not include sufficient numbers of subjects aged 65 and over to determine whether they respond differently from younger subjects. Other reported clinical experience has not identified differences in responses between the elderly and younger patients. In general, dose selection for an elderly patient should be cautious, usually starting at the low end of the dosing range, reflecting the greater frequency of decreased hepatic, renal, or cardiac function, and of concomitant disease or other drug therapy.

This drug is known to be substantially excreted by the kidney, and the risk of toxic reactions to this drug may be greater in patients with impaired renal function. Because elderly patients are more likely to have decreased renal function, care should be taken in dose selection, and it may be useful to monitor renal function.

ADVERSE REACTIONS

Gastrointestinal Disorders: Nausea and vomiting may occur; they are more frequent in ambulatory than in recumbent patients. Prolonged administration of Hydrocodone Polistirex and Chlorpheniramine Polistirex Extended-Release Oral Suspension may produce constipation.

General Disorders and Administration Site Conditions: Death.

Nervous System Disorders: Sedation, drowsiness, mental clouding, lethargy, impairment of mental and physical performance, anxiety, fear, dysphoria, euphoria, dizziness, psychic dependence, mood changes.

Renal and Urinary Disorders: Ureteral spasm, spasm of vesical sphincters, and urinary retention have been reported with opiates.

Respiratory, Thoracic and Mediastinal Disorders: Dryness of the pharynx, occasional tightness of the chest, and respiratory depression (see CONTRAINDICATIONS).

Hydrocodone Polistirex and Chlorpheniramine Polistirex Extended-Release Oral Suspension may produce dose-related respiratory depression by acting directly on brain stem respiratory centers (see OVERDOSAGE). Use of Hydrocodone Polistirex and Chlorpheniramine Polistirex Extended-Release Oral Suspension in children less than 6 years of age has been associated with fatal respiratory depression. Overdose with Hydrocodone Polistirex and Chlorpheniramine Polistirex Extended-Release Oral Suspension in children 6 years of age and older, in adolescents, and in adults has been associated with fatal respiratory depression.

Skin and Subcutaneous Tissue Disorders: Rash, pruritus.

DRUG ABUSE AND DEPENDENCE

Hydrocodone Polistirex and Chlorpheniramine Polistirex Extended-Release Oral Suspension is a Schedule II narcotic. Psychic dependence, physical dependence and tolerance may develop upon repeated administration of narcotics; therefore, Hydrocodone Polistirex and Chlorpheniramine Polistirex Extended-Release Oral Suspension should be prescribed and administered with caution. However, psychic dependence is unlikely to develop when Hydrocodone Polistirex and Chlorpheniramine Polistirex Extended-Release Oral Suspension is used for a short time for the treatment of cough. Physical dependence, the condition in which continued administration of the drug is required to prevent the appearance of a withdrawal syndrome, assumes clinically significant proportions only after several weeks of continued oral narcotic use, although some mild degree of physical dependence may develop after a few days of narcotic therapy.

OVERDOSAGE

Signs and Symptoms

Serious overdosage with hydrocodone is characterized by respiratory depression (a decrease in respiratory rate and/or tidal volume, Cheyne-Stokes respiration, cyanosis), extreme somnolence progressing to stupor or coma, skeletal muscle flaccidity, cold and clammy skin, and sometimes bradycardia and hypotension. Although miosis is characteristic of narcotic overdose, mydriasis may occur in terminal narcosis or severe hypoxia. In severe overdosage apnea, circulatory collapse, cardiac arrest and death may occur. The manifestations of chlorpheniramine overdosage may vary from central nervous system depression to stimulation.

Treatment

Primary attention should be given to the reestablishment of adequate respiratory exchange through provision of a patent airway and the institution of assisted or controlled ventilation. The narcotic antagonist naloxone hydrochloride is a specific antidote for respiratory depression which may result from overdosage or unusual sensitivity to narcotics including hydrocodone. Therefore, an appropriate dose of naloxone hydrochloride should be administered, preferably by the intravenous route, simultaneously with efforts at respiratory resuscitation. Since the duration of action of hydrocodone in this formulation may exceed that of the antagonist, the patient should be kept under continued surveillance and repeated doses of the antagonist should be administered as needed to maintain adequate respiration. For further information, see full prescribing information for naloxone hydrochloride. An antagonist should not be administered in the absence of clinically significant respiratory depression. Oxygen, intravenous fluids, vasopressors and other supportive measures should be employed as indicated. Gastric emptying may be useful in removing unabsorbed drug.

DOSAGE AND ADMINISTRATION

It is important that Hydrocodone Polistirex and Chlorpheniramine Polistirex Extended-Release Oral Suspension is measured with an accurate measuring device (see PRECAUTIONS, Information for Patients).

A dosing spoon is provided with the 4 oz (118 mL) packaged product. One side of the spoon is for a 2.5 mL dose. The other side of the spoon is for a 5 mL dose. Fill to level the side of the spoon for the dose that has been prescribed. Do not overfill. Rinse with water after each use.

For prescriptions where a dosing spoon is not provided, a pharmacist can provide an appropriate measuring device and can provide instructions for measuring the correct dose. A household teaspoon is not an accurate measuring device and could lead to overdosage.

Each 5 mL of Hydrocodone Polistirex and Chlorpheniramine Polistirex Extended-Release Oral Suspension contains hydrocodone polistirex equivalent to 10 mg hydrocodone bitartrate, and chlorpheniramine polistirex equivalent to 8 mg chlorpheniramine maleate. Shake well before using. Rinse the measuring device with water after each use.

Adults and Children 12 Years and Older

5 mL every 12 hours; do not exceed 10 mL in 24 hours.

Children 6 to 11 Years of Age

2.5 mL every 12 hours; do not exceed 5 mL in 24 hours.

This medicine is contraindicated in children under 6 years of age (see CONTRAINDICATIONS).

HOW SUPPLIED

Product: 17856-0301

NDC: 17856-0301-1 5 mL in a CUP

Manufactured by: Neos Therapeutics, LP

Grand Prairie, TX 75050

U.S. Patent 8,470,375; 8,512,759; 8,318, 210; 7,871,645; 8,329,224; 8,343,546 PIN030104 05/16

PATIENT INFORMATION

Hydrocodone Polistirex and Chlorpheniramine Polistirex
Extended-Release Oral Suspension CII

Read this Patient Information before you start taking Hydrocodone Polistirex and Chlorpheniramine Polistirex Extended-Release Oral Suspension and each time you get a refill. There may be new information. This information does not take the place of talking to your doctor about your medical condition or your treatment.

What is Hydrocodone Polistirex and Chlorpheniramine Polistirex Extended-Release Oral Suspension?

Hydrocodone Polistirex and Chlorpheniramine Polistirex Extended-Release Oral Suspension is a prescription medicine used to treat cough and upper respiratory symptoms you can have with allergies or a cold. Hydrocodone Polistirex and Chlorpheniramine Polistirex Extended-Release Oral Suspension is for adults and children age 6 years and older.

Hydrocodone Polistirex and Chlorpheniramine Polistirex Extended-Release Oral Suspension contains two medicines, hydrocodone and chlorpheniramine. Hydrocodone is a narcotic cough suppressant. Chlorpheniramine is an antihistamine.

Hydrocodone Polistirex and Chlorpheniramine Polistirex Extended-Release Oral Suspension is a controlled substance (CII) because it contains hydrocodone that can be a target for people who abuse prescription medicines or street drugs. Keep your Hydrocodone Polistirex and Chlorpheniramine Polistirex Extended-Release Oral Suspension in a safe place, to protect it from theft. Never give your Hydrocodone Polistirex and Chlorpheniramine Polistirex Extended-Release Oral Suspension to anyone else, because it may cause death or harm them. Selling or giving away this medicine is against the law.

Who should not take Hydrocodone Polistirex and Chlorpheniramine Polistirex Extended-Release Oral Suspension?

Do not take Hydrocodone Polistirex and Chlorpheniramine Polistirex Extended-Release Oral Suspension if you:

- are allergic to any of the ingredients in Hydrocodone Polistirex and Chlorpheniramine Polistirex Extended-Release Oral Suspension. See the end of this leaflet for a complete list of ingredients in Hydrocodone Polistirex and Chlorpheniramine Polistirex Extended-Release Oral Suspension.
- are a child under 6 years old. Hydrocodone Polistirex and Chlorpheniramine Polistirex Extended-Release Oral Suspension can cause a decreased rate of breathing (respiratory depression) which can lead to death.

What should I tell my doctor before taking Hydrocodone Polistirex and Chlorpheniramine Polistirex Extended-Release Oral Suspension?

Before you take Hydrocodone Polistirex and Chlorpheniramine Polistirex Extended-Release Oral Suspension, tell your doctor if you:

- have lung or breathing problems
- have had a head injury
- have pain in your belly (abdomen)
- have eye problems, such as glaucoma
- have prostate problems
- have problems with your urinary tract (urethral stricture)
- plan to have surgery
- abuse alcohol
- have kidney or liver problems
- have thyroid problems, such as hypothyroidism
- are pregnant or plan to become pregnant. If you take Hydrocodone Polistirex and Chlorpheniramine Polistirex Extended-Release Oral Suspension regularly before your baby is born, your newborn baby may have withdrawal symptoms because their body has become used to the medicine. Symptoms of withdrawal in a newborn baby may include:
  - irritability
  - crying more than usual
  - shaking (tremors)
  - jitteriness
  - breathing faster than normal
  - diarrhea or more stools than normal
  - sneezing
  - yawning
  - vomiting
  - fever

If you take Hydrocodone Polistirex and Chlorpheniramine Polistirex Extended-Release Oral Suspension regularly before your baby is born, your baby could have breathing problems.

- are breastfeeding or plan to breastfeed. You and your doctor should decide if you will take Hydrocodone Polistirex and Chlorpheniramine Polistirex Extended-Release Oral Suspension or breastfeed. You should not do both.

Tell your doctor about all of the medicines you take, including prescription and nonprescription medicines, vitamins, and herbal supplements.

Using Hydrocodone Polistirex and Chlorpheniramine Polistirex Extended-Release Oral Suspension with certain other medicines may affect each other. Using Hydrocodone Polistirex and Chlorpheniramine Polistirex Extended-Release Oral Suspension with other medicines can cause serious side effects.

Especially tell your doctor if you:

- take pain medicines such as narcotics
- take cold or allergy medicines that contain antihistamines or cough suppressants
- take medicines for mental illness (anti-psychotics, anti-anxiety)
- drink alcohol
- take medicines for depression including monoamine oxidase inhibitors (MAOIs)
- take medicines for stomach or intestine problems

Know the medicines you take. Keep a list of them to show your doctor and pharmacist when you get a new medicine.

How should I take Hydrocodone Polistirex and Chlorpheniramine Polistirex Extended-Release Oral Suspension?

- Take Hydrocodone Polistirex and Chlorpheniramine Polistirex Extended-Release Oral Suspension exactly as your doctor tells you.
- Shake the Hydrocodone Polistirex and Chlorpheniramine Polistirex Extended-Release Oral Suspension bottle well before you use it.
- Do not mix Hydrocodone Polistirex and Chlorpheniramine Polistirex Extended-Release Oral Suspension with other fluids or medicines. Mixing may change how Hydrocodone Polistirex and Chlorpheniramine Polistirex Extended-Release Oral Suspension works.
- Hydrocodone Polistirex and Chlorpheniramine Polistirex Extended-Release Oral Suspension can be taken with or without food.
- Only measure Hydrocodone Polistirex and Chlorpheniramine Polistirex Extended-Release Oral Suspension with the dosing spoon that comes with your prescription. See Figure A. If you do not have a dosing spoon for your medicine, ask your pharmacist to give you a measuring device to help you measure the correct amount of Hydrocodone Polistirex and Chlorpheniramine Polistirex Extended-Release Oral Suspension. Do not use a household teaspoon to measure your medicine. You may accidently take too much.
  - One side of the dosing spoon is marked for a 2.5 mL dose. The other side of the spoon is marked for a 5 mL dose. Find the side of the spoon that has the dose you are taking.
  - Fill that side of the spoon so the medicine is level with the rim of the spoon. Do not overfill the spoon.
  - Rinse the spoon with water after each use.

Figure A

- If you take too much Hydrocodone Polistirex and Chlorpheniramine Polistirex Extended-Release Oral Suspension, call your doctor or go to the nearest hospital emergency room right away.

What should I avoid while taking Hydrocodone Polistirex and Chlorpheniramine Polistirex Extended-Release Oral Suspension?

- Hydrocodone Polistirex and Chlorpheniramine Polistirex Extended-Release Oral Suspension can cause you to be drowsy. Do not drive a car or use machinery while you take Hydrocodone Polistirex and Chlorpheniramine Polistirex Extended-Release Oral Suspension until you know how it affects you.
- Do not drink alcohol while taking Hydrocodone Polistirex and Chlorpheniramine Polistirex Extended-Release Oral Suspension. Drinking alcohol can increase your chances of having serious side effects.

What are the possible side effects of Hydrocodone Polistirex and Chlorpheniramine Polistirex Extended-Release Oral Suspension?

Hydrocodone Polistirex and Chlorpheniramine Polistirex Extended-Release Oral Suspension may cause serious side effects, including:

- Decreased breathing (respiratory depression) which can lead to death. Call your doctor or get emergency treatment right away if you have:
  - shallow or slow breathing
  - confusion
  - excessive sleepiness
- drowsiness leading to inability to think clearly or do normal physical activities
- bowel problems, including constipation and bowel obstruction

The most common side effects of Hydrocodone Polistirex and Chlorpheniramine Polistirex Extended-Release Oral Suspension are:

- nausea and vomiting
- constipation
- nervous system problems (anxiety, fear, dizziness, mood changes)
- urinary tract problems
- dry throat
- chest tightness

Tell your doctor if you have any side effect that bothers you or that does not go away.

These are not all the possible side effects of Hydrocodone Polistirex and Chlorpheniramine Polistirex Extended-Release Oral Suspension. For more information, ask your doctor or pharmacist.

Call your doctor for medical advice about side effects. You may report side effects to FDA at 1-800-FDA-1088.

How should I store Hydrocodone Polistirex and Chlorpheniramine Polistirex Extended-Release Oral Suspension?

- Store Hydrocodone Polistirex and Chlorpheniramine Polistirex Extended-Release Oral Suspension in a safe place at 68°F to 77°F (20°C to 25°C).
- Safely throw away medicine that is out of date or no longer needed.
- Keep Hydrocodone Polistirex and Chlorpheniramine Polistirex Extended-Release Oral Suspension and all medicines out of the reach of children.

General information about Hydrocodone Polistirex and Chlorpheniramine Polistirex Extended-Release Oral Suspension

Medicines are sometimes prescribed for purposes other than those listed in a Patient Information Leaflet. Do not use Hydrocodone Polistirex and Chlorpheniramine Polistirex Extended-Release Oral Suspension for a condition for which it was not prescribed. Do not give Hydrocodone Polistirex and Chlorpheniramine Polistirex Extended-Release Oral Suspension to other people, even if they have the same condition. It may harm them and it is against the law.

This Patient Information Leaflet summarizes the most important information about Hydrocodone Polistirex and Chlorpheniramine Polistirex Extended-Release Oral Suspension. If you would like more information, talk with your doctor. You can ask your doctor or pharmacist for information about Hydrocodone Polistirex and Chlorpheniramine Polistirex Extended-Release Oral Suspension that is written for healthcare professionals.

For more information about Hydrocodone Polistirex and Chlorpheniramine Polistirex Extended-Release Oral Suspension call 1-(888)-319-1789.

What are the ingredients in Hydrocodone Polistirex and Chlorpheniramine Polistirex Extended-Release Oral Suspension?

Active Ingredient: hydrocodone polistirex and chlorpheniramine polistirex.

Inactive Ingredients: Purified Water, High Fructose Corn Syrup, Sucrose, Propylene Glycol, Xanthan Gum, Vegetable (Corn) Oil, Methylparaben, Polysorbate 80, Ascorbic Acid, Propylparaben, Ethylcellulose, Sorbitol, Dibutyl Sebacate, Natural Mango Flavor, D&C Yellow No. 10, FD&C Yellow No. 6, Sodium Benzoate, and Phosphoric Acid.

Hydrocodone Polistirex and Chlorpheniramine Polistirex Extended-Release Oral Suspension
Manufactured by:
Neos Therapeutics, LP
Grand Prairie, TX 75050

This patient information has been approved by the U.S. Food and Drug Administration.

U.S. Patent 8,470,375; 8,512,759; 8,318, 210; 7,871,645; 8,329,224; 8,343,546 PIN030104 05/16